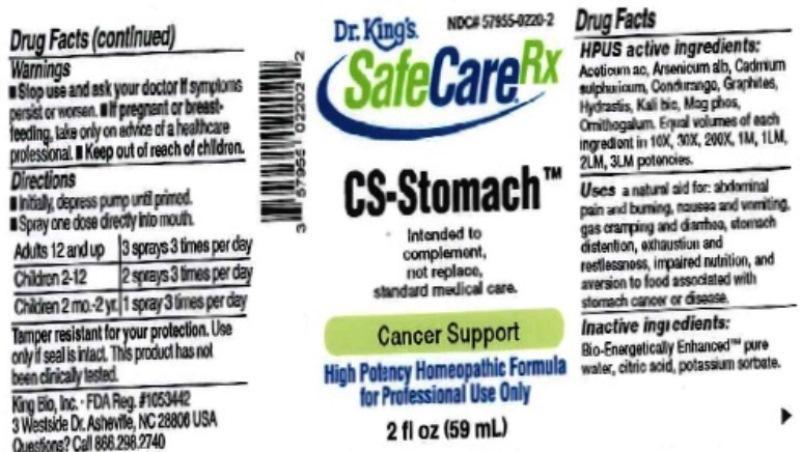 DRUG LABEL: CS Stomach
NDC: 57955-0220 | Form: LIQUID
Manufacturer: King Bio Inc.
Category: homeopathic | Type: HUMAN OTC DRUG LABEL
Date: 20161209

ACTIVE INGREDIENTS: ACETIC ACID 10 [hp_X]/59 mL; ARSENIC TRIOXIDE 10 [hp_X]/59 mL; CADMIUM SULFATE 10 [hp_X]/59 mL; MARSDENIA CONDURANGO BARK 10 [hp_X]/59 mL; GRAPHITE 10 [hp_X]/59 mL; GOLDENSEAL 10 [hp_X]/59 mL; POTASSIUM DICHROMATE 10 [hp_X]/59 mL; MAGNESIUM PHOSPHATE, DIBASIC TRIHYDRATE 10 [hp_X]/59 mL; ORNITHOGALUM UMBELLATUM 10 [hp_X]/59 mL
INACTIVE INGREDIENTS: WATER; ANHYDROUS CITRIC ACID; POTASSIUM SORBATE

CS Stomach™

ACTIVE INGREDIENT

Drug Facts__________________________________________________________________________________________________________

HPUS active ingredients: Aceticum acidum, Arsenicum album, Cadmium sulphuricum, Condurango, Graphites, Hydrastis canadensis, Kali bichromicum, Magnesia phosphorica, Ornithogalum Umbellatum. Equal volumes of each ingredient in 10X, 30X, 200X, 1M, 1LM, 2LM, 3LM potencies.

INDICATIONS AND USAGE

Uses a natural aid for abdominal pain and burning, nausea and vomiting, gas cramping and diarrhea, stomach distention, exhaustion and restlessness, impaired nutrition, and aversion to food associated with stomach cancer or disease.

Inactive Ingredients:

Bio-Energetically Enhanced™ pure water, citric acid and potassium sorbate.

Warnings

- Stop use and ask your doctor if symptoms persist or worsen.
- If pregnant or breast-feeding, take only on advice of a healthcare professional.

- Keep out of reach of children.

Directions

- Initially, depress pump until primed.
- Spray one dose directly into mouth.
- Adults 12 and up: 3 sprays 3 times per day.
- Children 2-12 years: 2 sprays 3 times per day.
- Children 2 mo-2 yr: 1 spray 3 times per day.

OTHER SAFETY INFORMATION

Tamper resistant for your protection. Use only if safety seal is intact. This product has not been clinically tested.

PURPOSE

Uses a natural aid for:

- abdominal pain and burning
- nausea
- vomiting,
- gas cramping
- diarrhea
- stomach distention
- exhaustion
- restlessness
- impaired nutrition
- aversion to food associated with stomach cancer or disease